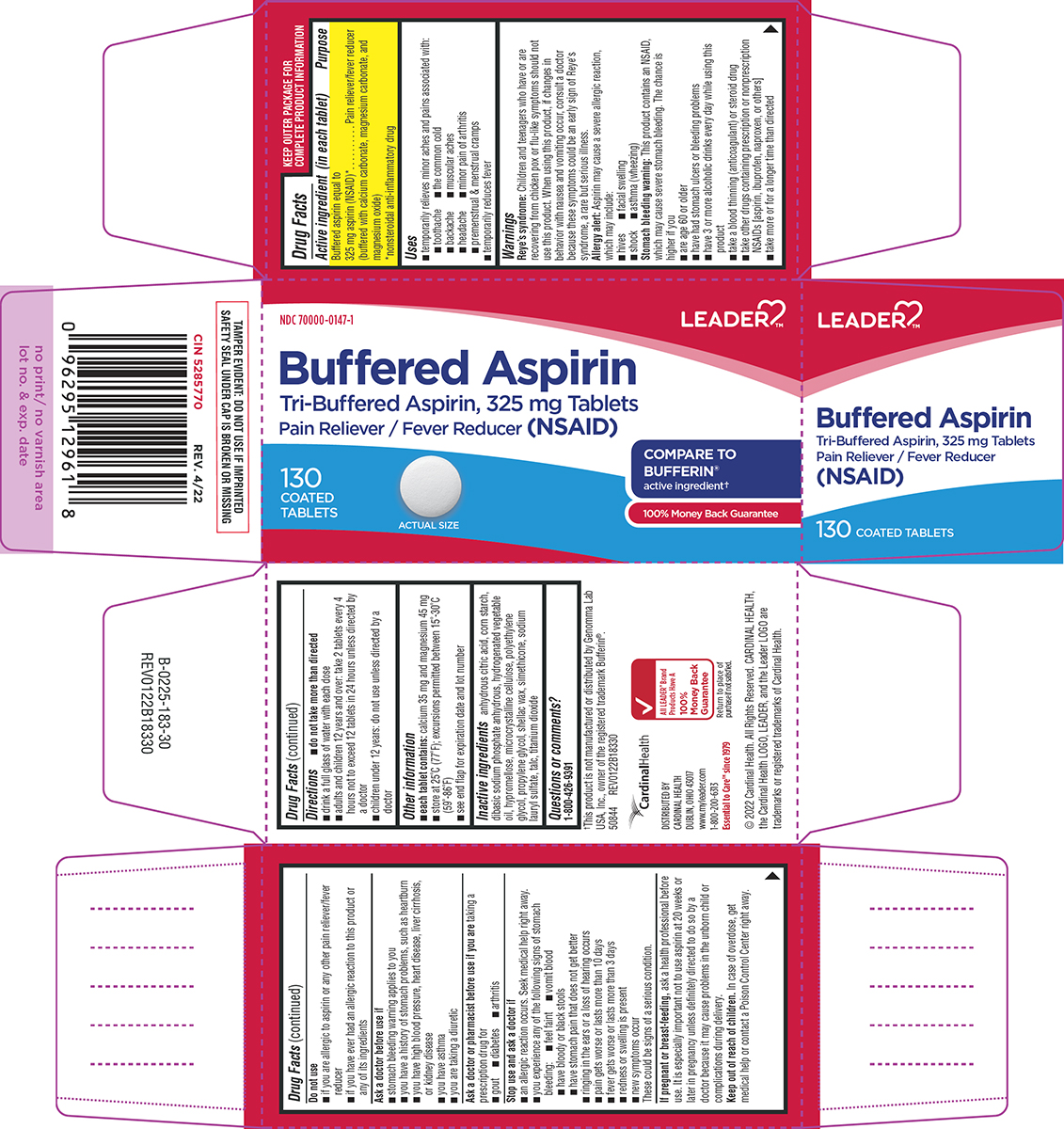 DRUG LABEL: Buffered Aspirin
NDC: 70000-0147 | Form: TABLET, FILM COATED
Manufacturer: Cardinal Health 110, LLC. DBA Leader
Category: otc | Type: HUMAN OTC DRUG LABEL
Date: 20260206

ACTIVE INGREDIENTS: ASPIRIN 325 mg/1 1
INACTIVE INGREDIENTS: ANHYDROUS CITRIC ACID; STARCH, CORN; SODIUM PHOSPHATE, DIBASIC, ANHYDROUS; HYDROGENATED COTTONSEED OIL; HYPROMELLOSE, UNSPECIFIED; MICROCRYSTALLINE CELLULOSE; POLYETHYLENE GLYCOL, UNSPECIFIED; PROPYLENE GLYCOL; SHELLAC; DIMETHICONE 410; SILICON DIOXIDE; SODIUM LAURYL SULFATE; TALC; TITANIUM DIOXIDE

Leader 44-183

Active ingredient (in each tablet)

Buffered aspirin equal to 325 mg aspirin (NSAID)*
(buffered with calcium carbonate, magnesium carbonate, and magnesium oxide)
*nonsteroidal anti-inflammatory drug

Purpose

Pain reliever/fever reducer

Uses

- temporarily relieves minor aches and pains associated with:
  - toothache
  - minor pain of arthritis
  - backache
  - the common cold
  - headache
  - muscular aches
  - premenstrual & menstrual cramps
- temporarily reduces fever

Warnings

Reye’s syndrome: Children and teenagers who have or are recovering from chicken pox or flu-like symptoms should not use this product. When using this product, if changes in behavior with nausea and vomiting occur, consult a doctor because these symptoms could be an early sign of Reye's syndrome, a rare but serious illness.

Allergy alert: Aspirin may cause a severe allergic reaction, which may include:

- shock
- hives
- asthma (wheezing)
- facial swelling

Stomach bleeding warning: This product contains an NSAID, which may cause severe stomach bleeding. The chance is higher if you

- have had stomach ulcers or bleeding problems
- have 3 or more alcoholic drinks every day while using this product
- are age 60 or older
- take a blood thinning (anticoagulant) or steroid drug
- take other drugs containing prescription or nonprescription NSAIDs [aspirin, ibuprofen, naproxen, or others]
- take more or for a longer time than directed

Do not use

- if you are allergic to aspirin or any other pain reliever/fever reducer
- if you have ever had an allergic reaction to this product or any of its ingredients

Ask a doctor before use if

- stomach bleeding warning applies to you
- you have a history of stomach problems, such as heartburn
- you have asthma
- you are taking a diuretic
- you have high blood pressure, heart disease, liver cirrhosis, or kidney disease

Ask a doctor or pharmacist before use if you are

taking a prescription drug for

- gout
- diabetes
- arthritis

Stop use and ask a doctor if

- an allergic reaction occurs. Seek medical help right away.
- you experience any of the following signs of stomach bleeding:
  - feel faint
  - vomit blood
  - have bloody or black stools
  - have stomach pain that does not get better
- ringing in the ears or a loss of hearing occurs
- pain gets worse or lasts more than 10 days
- fever gets worse or lasts more than 3 days
- redness or swelling is present
- new symptoms occur

These could be signs of a serious condition.

If pregnant or breast-feeding,

ask a health professional before use. It is especially important not to use aspirin at 20 weeks or later in pregnancy unless definitely directed to do so by a doctor because it may cause problems in the unborn child or complications during delivery.

Keep out of reach of children.

In case of overdose, get medical help or contact a Poison Control Center right away.

Directions

- do not take more than directed
- drink a full glass of water with each dose
- adults and children 12 years and over: take 2 tablets every 4 hours not to exceed 12 tablets in 24 hours unless directed by a doctor
- children under 12 years: do not use unless directed by a doctor

Other information

- each tablet contains: calcium 35 mg and magnesium 45 mg
- store at 25°C (77°F); excursions permitted between 15°-30°C (59°-86°F)
- see end flap for expiration date and lot number

Inactive ingredients

anhydrous citric acid, corn starch, dibasic sodium phosphate anhydrous, hydrogenated vegetable oil, hypromellose, microcrystalline cellulose, polyethylene glycol, propylene glycol, shellac wax, simethicone, sodium lauryl sulfate, talc, titanium dioxide

Questions or comments?

1-800-426-9391

Principal display panel

Leader™

NDC 70000-0147-1

Buffered Aspirin
Tri-Buffered Aspirin, 325 mg Tablets
Pain Reliever / Fever Reducer (NSAID)

130
COATED
TABLETS

ACTUAL SIZE

COMPARE TO
BUFFERIN®
active ingredient†

100% Money Back Guarantee

TAMPER EVIDENT: DO NOT USE IF IMPRINTED
SAFETY SEAL UNDER CAP IS BROKEN OR MISSING

CIN 5285770 REV. 4/22

†This product is not manufactured or distributed by Genomma Lab
USA, Inc., owner of the registered trademark Bufferin®.
50844 REV0122B18330

DISTRIBUTED BY
CARDINAL HEALTH
DUBLIN, OHIO 43017
www.myleader.com
1-800-200-6313
Essential to Care™ since 1979

All LEADERTM Brand
Products Have A
100%
Money Back
Guarantee

© 2022 Cardinal Health. All Rights Reserved. CARDINAL HEALTH,
the Cardinal Health LOGO, LEADER, and the Leader LOGO are
trademarks or registered trademarks of Cardinal Health.

Leader 44-183